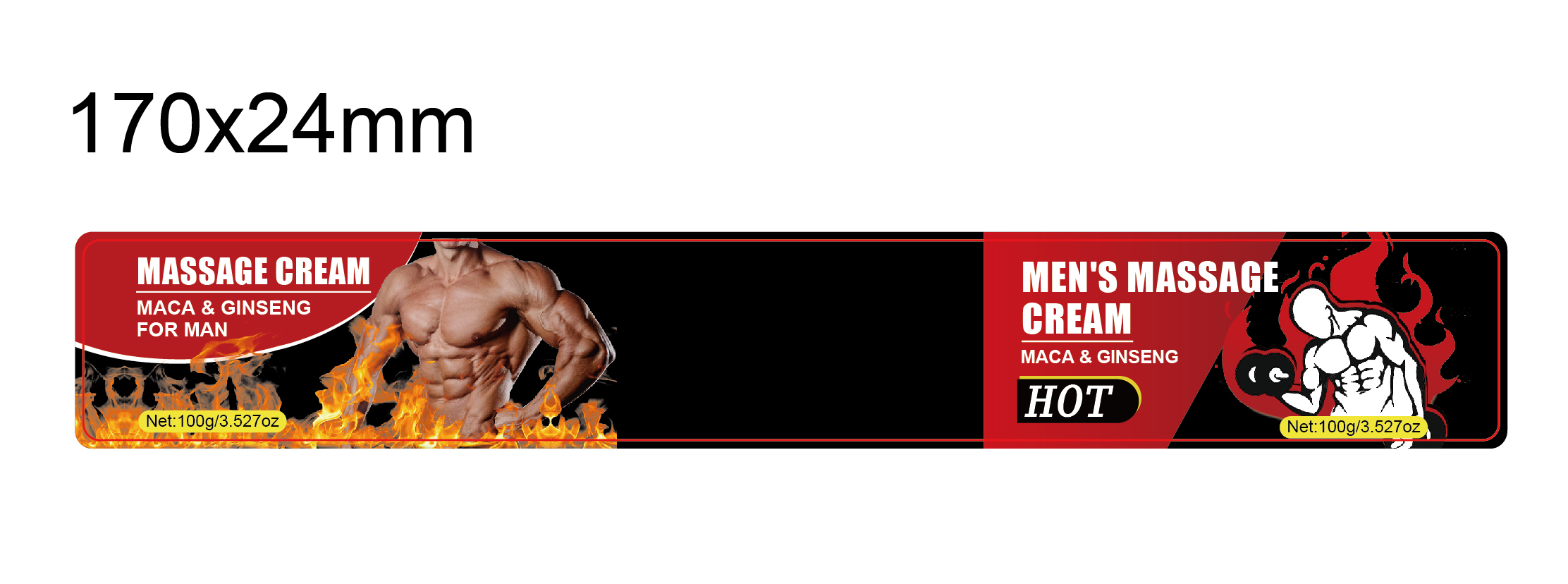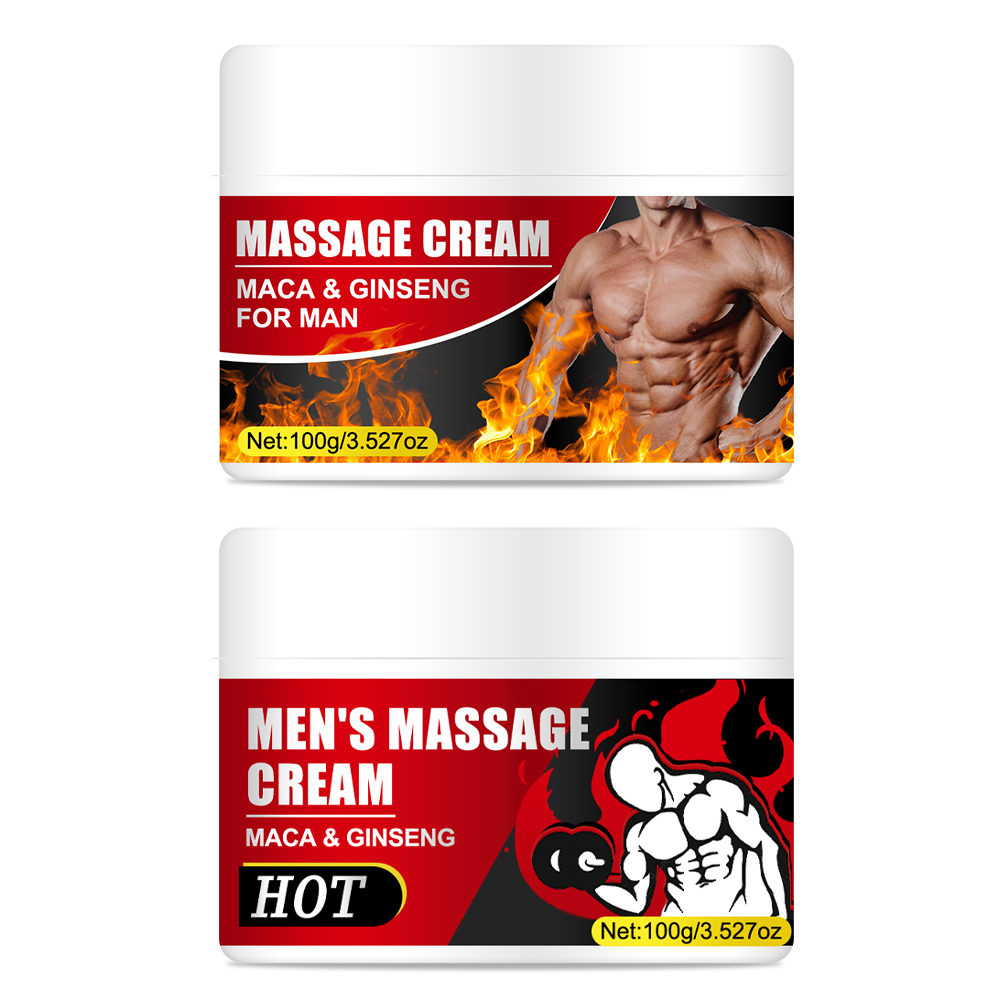 DRUG LABEL: Mens Massage Cream
NDC: 84025-214 | Form: CREAM
Manufacturer: Guangzhou Yanxi Biotechnology Co., Ltd
Category: otc | Type: HUMAN OTC DRUG LABEL
Date: 20241014

ACTIVE INGREDIENTS: PANTHENOL 3 mg/100 mL; GLYCERIN 5 mg/100 mL
INACTIVE INGREDIENTS: WATER

DOSAGE AND ADMINISTRATION

The method of using the cream is simple and convenient. Just clean the penis, apply it and gently massage to absorb. It will work in a short time.

WARNINGS

Keep out of children

INACTIVE INGREDIENT

Aqua

INDICATIONS AND USAGE

Short duration of sexual function

keep out of children

PURPOSE

The penis erection cream could make the dick thicker, larger, and longer. It can help you to increase feelings of desire and intensify climax.